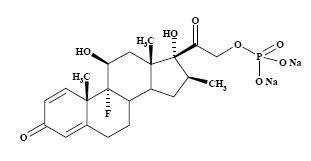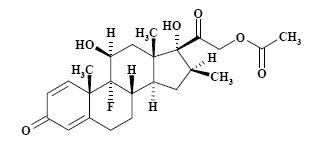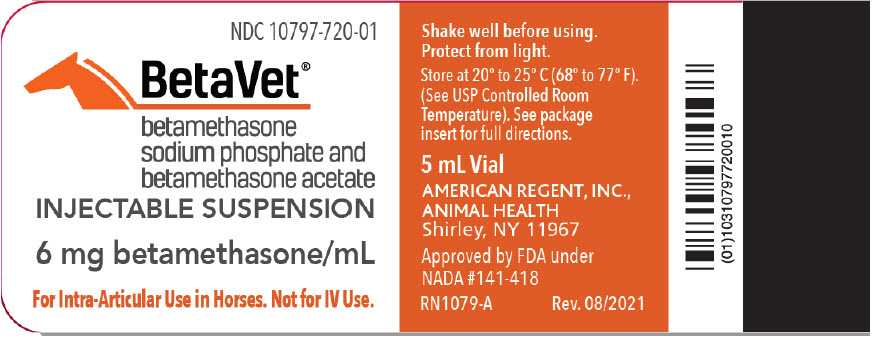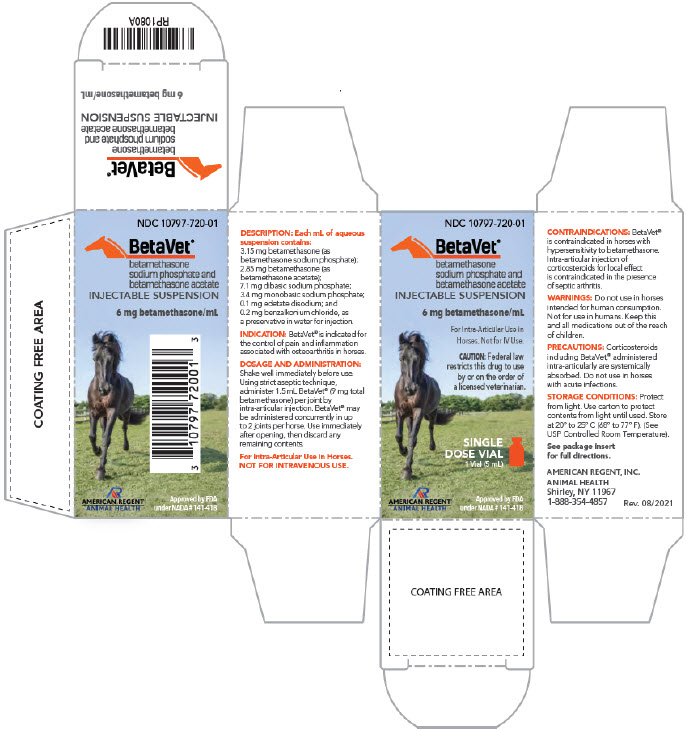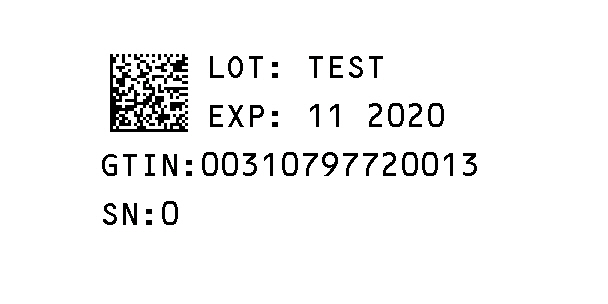 DRUG LABEL: BetaVet
NDC: 10797-720 | Form: INJECTION, SUSPENSION
Manufacturer: American Regent, Inc.
Category: animal | Type: PRESCRIPTION ANIMAL DRUG LABEL
Date: 20241007

ACTIVE INGREDIENTS: BETAMETHASONE ACETATE 2.85 mg/1 mL; BETAMETHASONE SODIUM PHOSPHATE 3.15 mg/1 mL
INACTIVE INGREDIENTS: SODIUM PHOSPHATE, DIBASIC, ANHYDROUS 7.1 mg/1 mL; SODIUM PHOSPHATE, MONOBASIC, MONOHYDRATE 3.4 mg/1 mL; EDETATE DISODIUM 0.1 mg/1 mL; BENZALKONIUM CHLORIDE 0.2 mg/1 mL; WATER

BETAVET® (Betamethasone Sodium Phosphate and Betamethasone Acetate Injectable Suspension)

6 mg betamethasone per mL
For Intra-Articular (I.A.) Use in Horses

CAUTION: Federal law restricts this drug to use by or on the order of a licensed veterinarian.

DESCRIPTION

BETAVET® is a sterile aqueous suspension of betamethasone acetate in betamethasone sodium phosphate injection. The combined betamethasone content of the suspension is 6 mg/mL where each mL contains 3.15 mg betamethasone (as betamethasone sodium phosphate); 2.85 mg betamethasone (as betamethasone acetate); 7.1 mg dibasic sodium phosphate; 3.4 mg monobasic sodium phosphate; 0.1 mg edetate disodium; and 0.2 mg benzalkonium chloride, as a preservative in water for injection. The pH is adjusted to between 6.8 and 7.2.

The formula for betamethasone sodium phosphate is C22H28FNa2O8P and it has a molecular weight of 516.41. Chemically, it is 9-Fluoro-11β,17,21-trihydroxy-16β-methylpregna-1,4-diene-3,20-dione 21-(disodium phosphate).

The formula for betamethasone acetate is C24H31FO6 and it has a molecular weight of 434.50. Chemically, it is 9-Fluoro-11β,17,21-trihydroxy-16β-methylpregna-1,4-diene-3,20-dione 21-acetate.

The chemical structures for betamethasone sodium phosphate and betamethasone acetate are as follows:

betamethasone sodium phosphate
betamethasone acetate

Betamethasone sodium phosphate is a white to practically white, odorless powder, and is hygroscopic. It is freely soluble in water and in methanol, but is practically insoluble in acetone and in chloroform.

Betamethasone acetate is a white to creamy white, odorless powder that sinters and resolidifies at about 165ºC, and remelts at about 200ºC-220ºC with decomposition. It is practically insoluble in water, but freely soluble in acetone, and is soluble in alcohol and in chloroform.

INDICATION

BETAVET is indicated for the control of pain and inflammation associated with osteoarthritis in horses.

DOSAGE AND ADMINISTRATION

Shake well immediately before use.

Using strict aseptic technique, administer 1.5 mL BETAVET (9 mg total betamethasone) per joint by intra-articular injection. BETAVET may be administered concurrently in up to 2 joints per horse.

Use immediately after opening, then discard any remaining contents.

CONTRAINDICATIONS

BETAVET is contraindicated in horses with hypersensitivity to betamethasone.

Intra-articular injection of corticosteroids for local effect is contraindicated in the presence of septic arthritis.

WARNINGS

Do not use in horses intended for human consumption.

Clinical and experimental data have demonstrated that corticosteroids administered orally or parenterally to animals may induce the first stage of parturition when administered during the last trimester of pregnancy and may precipitate premature parturition followed by dystocia, fetal death, retained placenta, and metritis.

Additionally, corticosteroids administered to dogs, rabbits and rodents during pregnancy have resulted in cleft palate in offspring. Corticosteroids administered to dogs during pregnancy have also resulted in other congenital anomalies including deformed forelegs, phocomelia and anasarca. Therefore, before use of corticosteroids in pregnant animals, the possible benefits to the pregnant animal should be weighed against potential hazards to its developing embryo or fetus.

Human Warnings: Not for use in humans. For use in animals only. Keep this and all medications out of the reach of children. Consult a physician in the case of accidental human exposure.

PRECAUTIONS

Corticosteroids, including BETAVET, administered intraarticularly are systemically absorbed. Do not use in horses with acute infections.

Acute moderate to severe exacerbation of pain, further loss of joint motion, fever, or malaise within several days following intra-articular injection may indicate a septic process. Because of the anti-inflammatory action of corticosteroids, signs of infection in the treated joint may be masked. Appropriate examination of joint fluid is necessary to exclude a septic process. If a bacterial infection is present, appropriate antibacterial therapy should be instituted immediately. Additional doses of corticosteroids should not be administered until joint sepsis has been definitively ruled out.

Due to the potential for exacerbation of clinical signs of laminitis, glucocorticoids should be used with caution in horses with a history of laminitis, or horses otherwise at a higher risk for laminitis.

Use with caution in horses with chronic nephritis, equine pituitary pars intermedia dysfunction (PPID), and congestive heart failure.

Concurrent use of other anti-inflammatory drugs, such as NSAIDs or other corticosteroids, should be approached with caution. Due to the potential for systemic exposure, concomitant use of NSAIDs and corticosteroids may increase the risk of gastrointestinal, renal, and other toxicity. Consider appropriate wash out times prior to administering additional NSAIDs or corticosteroids.

ADVERSE REACTIONS

Adverse reactions reported during a field study of 239 horses of various breeds which had been administered either BETAVET (n=119) or a saline control (n=120) are summarized in Table 1. One BETAVET treated horse was removed from the study for onset of acute non-weight bearing lameness on Day 4. Treatment for presumed joint sepsis was instituted immediately, but the horse was eventually euthanized several weeks later due to a thromboembolic event associated with prolonged intravenous catheter placement. One BETAVET treated horse developed bilateral forelimb lameness on Day 8, with snow packed in the shoes and poor hoof conformation noted by the investigator. The horse was diagnosed with laminitis. Radiographs showed no abnormalities, and the horse was sound shortly after shoeing changes were implemented.

Table 1. Adverse Reactions

Adverse Reaction | Number (%) of BETAVET treated horses | Number (%) of saline treated horses
Acute joint effusion and/or local injection site swelling (within 2 days of injection) | 18 (15%) | 16 (13%)
Increased lameness (within the first 5 days) | 8 (6.7%) | 10 (8.3%)
Loose stool | 7 (5.9%) | 10 (8.3%)
Increased heat in joint | 3 (2.5%) | 6 (5%)
Depression | 7 (5.9%) | 2 (1.6%)
Agitation/anxiety | 5 (4.2%) | 3 (2.5%)
Delayed swelling of treated joint (5 or more days after injection) | 3 (2.5%) | 4 (3.3%)
Inappetance | 4 (3.4%) | 3 (2.5%)
Dry stool | 2 (1.7%) | 0 (0%)
Excessive sweating | 1 (0.8%) | 0 (0%)
Acute non-weight bearing lameness | 1 (0.8%) | 0 (0%)
Laminitis | 1 (0.8%) | 0 (0%)

CLINICAL PHARMACOLOGY

Betamethasone is a potent glucocorticoid steroid with anti-inflammatory and immunosuppressive properties. Depending upon their physico-chemical properties, drugs administered intra-articularly may enter the general circulation because the synovial joint cavity is in direct equilibrium with the surrounding blood supply. After the intra-articular administration of 9 mg BETAVET in horses, there were quantifiable concentrations of betamethasone (above 1.0 ng/mL) in the plasma. Maximum plasma concentrations (Cmax) and time to Cmax (Tmax) values ranged from 2.70 to 3.88 ng/mL and 4.5 to 8 hours, respectively. The effective plasma terminal elimination half-life ranged from 4 to 8 hours. The non-compartmental area-underthe curve to the limit of quantification (AUCLOQ) ranged from 29.24 to 42.96 hr*ng/mL. In contrast, most of the betamethasone disodium phosphate concentrations and all of the betamethasone acetate concentrations were below the limit of quantification in plasma.

EFFECTIVENESS

A negative control, randomized, masked field study provided data to evaluate the effectiveness of BETAVET administered at 1.5 mL (9 mg betamethasone) once intra-articularly for the control of pain and inflammation associated with osteoarthritis in horses. A total of 119 horses received BETAVET and 120 horses received saline. 229 horses were included in the final effectiveness analysis. Clinical success was defined as improvement in one lameness grade according to the AAEP lameness scoring system on Day 5 following treatment. Table 2 summarizes the clinical success and failure in each treatment group on Day 5. The success rate for horses in the BETAVET group was statistically significantly different (p=0.0061) than that in the saline group, with success rates of 75.73% and 52.52%, respectively (back-transformed from the logistic regression).

Table 2. Clinical Effectiveness Results

 | BETAVET (n=114) | Saline (n=115)
Number of Successes | 87 | 61
Number of Failures | 27 | 54

ANIMAL SAFETY

A 3-week target animal safety (TAS) study was conducted to evaluate the safety of BETAVET in mature, healthy horses. The study was designed with 4 treatment groups of 8 horses in each group. Treatment groups included a control (isotonic saline at a volume equivalent to the 4x group); 1X (0.0225 mg betamethasone per pound bodyweight; BETAVET); 2X (0.045 mg betamethasone per pound bodyweight; BETAVET) and 4X (0.09 mg betamethasone per pound bodyweight; BETAVET). Treatments were administered by intra-articular injection into the left middle carpal joint once every 5-days for 3 treatments.

Injection site reactions were the most common observations in all treatment groups. Injection site reactions were observed within 1 hour of dosing and included swelling at the injection site, lameness/stiffness of the left front limb, and flexing the left front knee at rest (see table 3).

Table 3. Incidence of Injection Site Reactions

Group | Total Swelling Observations | Excessive/ obvious swelling | Pain at injection site | Knee flexed at rest | Lame or stiff
0x | 14 | 1 | 0 | 0 | 0
1x | 6 | 1 | 0 | 0 | 0
2x | 11 | 2 | 0 | 0 | 0
4x | 18 | 10 | 3 | 3 | 2

The injection site reactions ranged from slight swelling (in many horses on multiple days in all treatment groups) to excessive fluid with swelling, pain, and lameness (4x group only). Injection site reactions were observed most commonly on treatment days, and generally decreased in number and severity over subsequent days. The incidence of injection site reactions increased after the second and third injection (number of abnormalities noted on day 10 > day 5 > day 0). In the BETAVET treated groups the number and severity of the injection site reactions were dose dependent. The 4X BETAVET group had the highest overall incidence of and severity of injection site reactions, which included heat, swelling, pain, bleeding, and holding the limb up at rest. The control group and 4X group (which received similar injection volumes) had a similar incidence of injection site reactions; however, the severity of reactions was greater in the 4X group.

Absolute neutrophils were statistically significantly higher in the BETAVET treated groups as compared to the control group. Trends toward a decrease in lymphocytes and eosinophils, and an increase in monocytes were identified in the BETAVET treated groups after the initial dose of BETAVET. Individual animal values for white blood cells generally remained within the reference range. BETAVET treated horses also had a trend toward increased blood glucose after the initial dose. Some individual animals showed mild increases in blood glucose above the reference range.

STORAGE CONDITIONS

Store at 20° to 25°C (68° to 77°F) (See USP Controlled Room Temperature). Protect from light. Use carton to protect contents from light until used.

HOW SUPPLIED

BETAVET, containing 30 mg betamethasone/5 mL (6 mg betamethasone/mL) in 5 mL vials.
NDC 10797-720-01 5 mL VIALS Packaged in boxes of 1

SHAKE WELL BEFORE USING
Approved by FDA under NADA # 141-418

AMERICAN REGENT, INC.
ANIMAL HEALTH
Shirley, NY 11967
(1-888-354-4857)
Rev. 8/2021

RQ1053-A

PRINCIPAL DISPLAY PANEL - CONTAINER LABEL

NDC 10797-720-01

BetaVet®
betamethasone sodium phosphate and betamethasone acetate

INJECTABLE SUSPENSION

6 mg betamethasone/mL
For Intra-Articular Use in Horses. Not for IV Use.

Shake well before using.
Protect from light.

Store at 20ºC to 25ºC (68º to 77ºF) (See USP Controlled Room Temperature).
See package insert for full directions.

5 mL Vial

AMERICAN REGENT, INC.
ANIMAL HEALTH
Shirley, NY 11967
Approved by FDA under NADA # 141-418

RN1079-A
Rev. 08/2021

PRINCIPAL DISPLAY PANEL - CARTON LABELING

NDC 10797-720-01

BetaVet®
betamethasone sodium phosphate and betamethasone acetate

INJECTABLE SUSPENSION
6 mg betamethasone/mL

For Intra-Articular Use in Horses. Not for IV Use.

CAUTION: Federal law restricts this drug to use by or on the order of a licensed veterinarian.
SINGLE DOSE VIAL
1 Vial (5 mL)

Approved by FDA under NADA # 141-418
AMERICAN REGENT, INC.
ANIMAL HEALTH